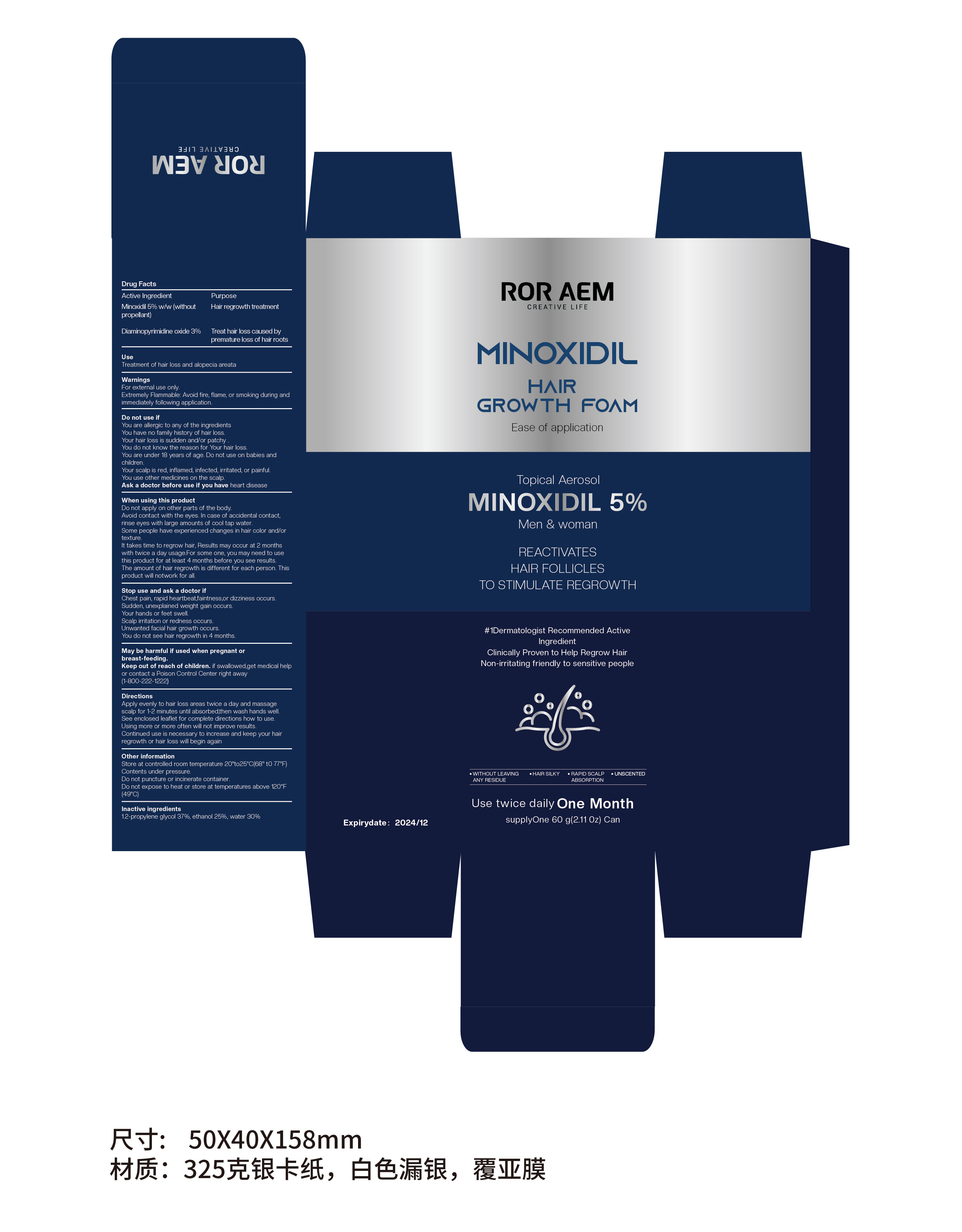 DRUG LABEL: MINOXIDIL HAIR GROWTH FOAM
NDC: 84315-001 | Form: AEROSOL, FOAM
Manufacturer: Guangzhou Yibai Technology Sarl
Category: otc | Type: HUMAN OTC DRUG LABEL
Date: 20240508

ACTIVE INGREDIENTS: DIAMINOPYRIMIDINE OXIDE 3 g/100 g; MINOXIDIL 5 g/100 g
INACTIVE INGREDIENTS: PROPYLENE GLYCOL; ALCOHOL; WATER

84315-001

ACTIVE INGREDIENT

Minoxidil 5% w/w (without propellant)

Diaminopyrimidine oxide 3%

PURPOSE

Hair regrowth treatment

Treat hair loss caused by premature loss of hair roots

INDICATIONS AND USAGE

Treatment of hair loss and alopecia areata

WARNINGS

For external use only.

Extremely Flammable: Avoid fire, flame, or smoking during and immediately following application.

DO NOT USE

You are allergic to any of the ingredients

You have no family history of hair loss.

Your hair loss is sudden and/or patchy.

You do not know the reason for Your hair loss.

You are under 18 years of age. Do not use on babies and children.

Your scalp is red, inflamed, infected, irritated, or painful.

You use other medicines on the scalp.

Ask a doctor before use if you have heart disease

WHEN USING

Do not apply on other parts of the body.

Avoid contact with the eyes. In case of accidental contact, rinse eyes with large amounts of cool tap water.

Some people have experienced changes in hair color and/or texture.

It takes time to regrow hair, Results may occur at 2 months with twice a day usage.For some one, you may need to use this product for at least 4 months before you see results.The amount of hair regrowth is different for each person. This product will notwork for all.

Stop use and ask a doctor if

Chest pain, rapid heartbeat,faintness,or dizziness occurs.

Sudden, unexplained weight gain occurs.

Your hands or feet swell.

Scalp irritation or redness occurs.

Unwanted facial hair growth occurs.

You do not see hair regrowth in 4 months.

KEEP OUT OF REACH OF CHILDREN

May be harmful if used when pregnant or breast-feeding.

Keep out of reach of children. if swallowed,get medical help or contact a Poison Control Center right away(1-800-222-1222)

DOSAGE AND ADMINISTRATION

Apply evenly to hair loss areas twice a day and massage scalp for 1-2 minutes until absorbed,then wash hands well.See enclosed leaflet for complete directions how to use.Using more or more often will not improve results.Continued use is necessary to increase and keep your hair regrowth or hair loss will begin again

STORAGE AND HANDLING

Store at controlled room temperature 20° to 25℃ (68° to 77°F) Contents under pressure.

Do not puncture or incinerate container.

Do not expose to heat or store at temperatures above 120°F (49℃)

INACTIVE INGREDIENT

1.2-propylene glycol 37%, ethanol 25%, water 30%